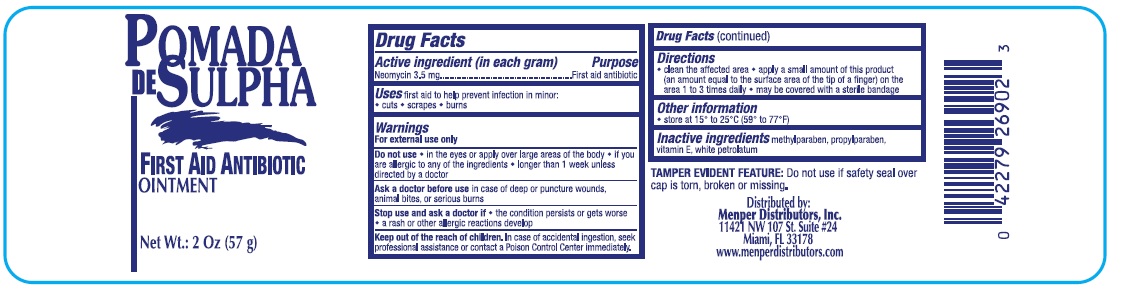 DRUG LABEL: Pomada de Sulfa
NDC: 53145-056 | Form: OINTMENT
Manufacturer: Menper Distributors, Inc.
Category: otc | Type: HUMAN OTC DRUG LABEL
Date: 20250722

ACTIVE INGREDIENTS: NEOMYCIN SULFATE 3.5 mg/1 g
INACTIVE INGREDIENTS: METHYLPARABEN; PROPYLPARABEN; PETROLATUM; VITAMIN E POLYETHYLENE GLYCOL SUCCINATE

Pomada de Sulfa

Active ingredient (in each gram)

Neomycin 3.5 mg

Purpose

First aid antibiotic

Uses

first aid to help prevent infection in minor

- cuts
- scrapes
- burns

Warnings

For external use only

Do not use

- in the eyes or apply over large areas of the body
- if you are allergic to any of the ingredients
- longer than 1 week unless directed by a doctor

Ask a doctor before usein case of deep or puncture wounds, animal bites, or serious burns

Stop use and ask a doctor if

- the condition persists or gets worse
- a rash or other allergic reactions develop

Keep out of reach of children. In case of accidental ingestion, seek professional assistance or contact a Poison Control Center immediately.

Directions

- clean the affected area
- apply a small amount of this product (an amount equal to the surface area of the tip of a finger) on the area 1 to 3 times daily
- may be covered with a sterile bandage

Inactive ingredients

methylparaben, propylparaben, vitamin E, white petrolatum

QUESTIONS

Menper Distributs, Inc.

11421 NW 107 St. Suite #24

Miami Fl 33178

www.menperdistributors.com